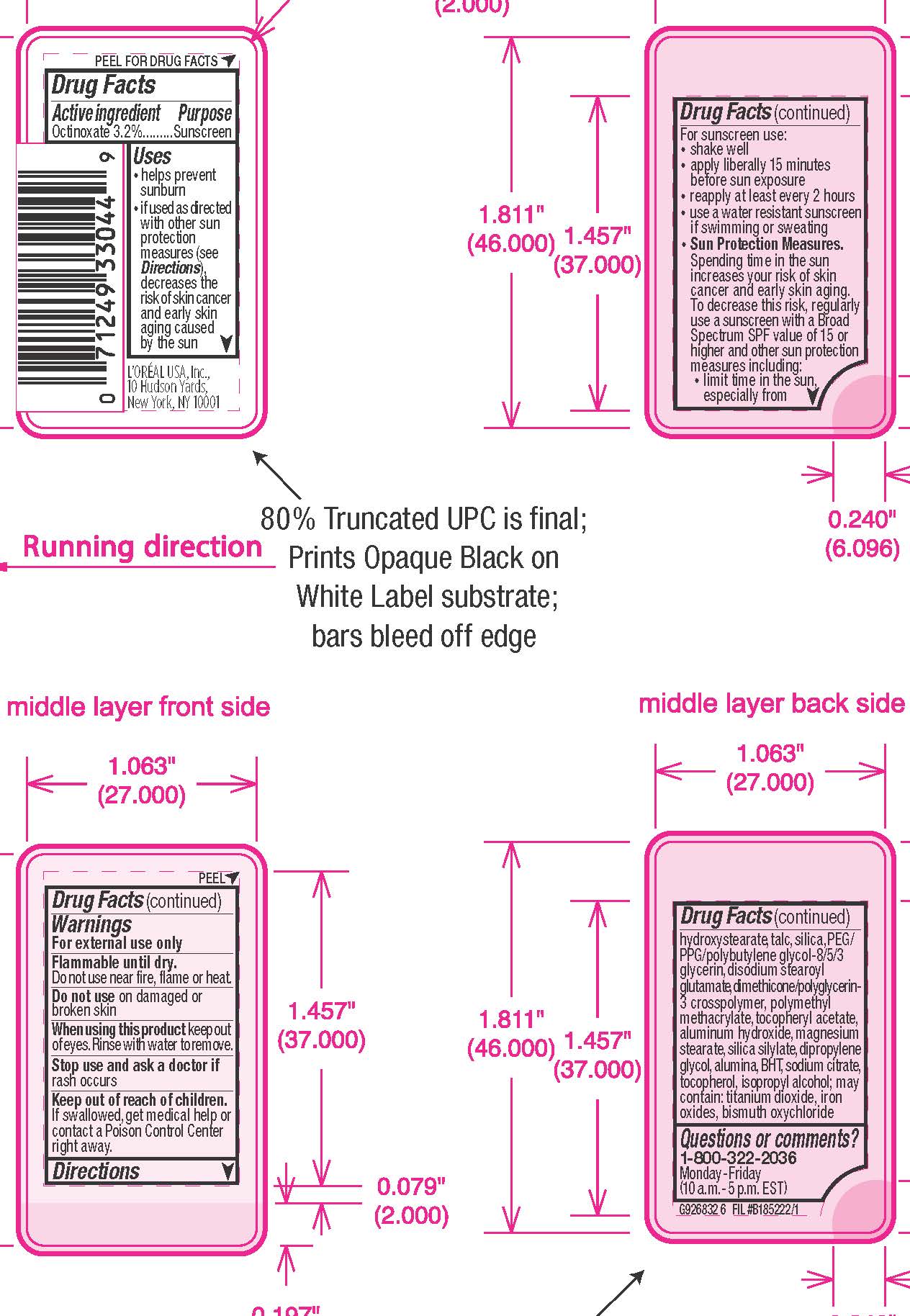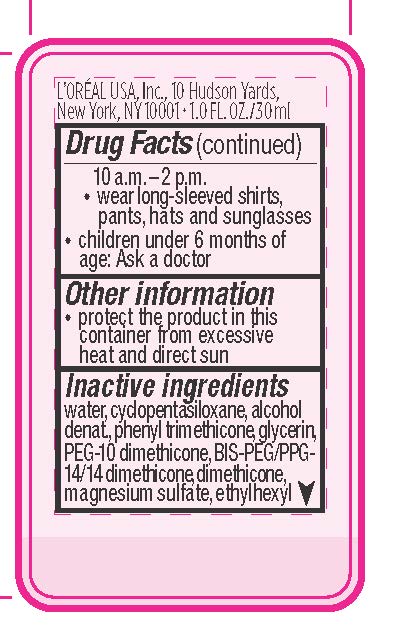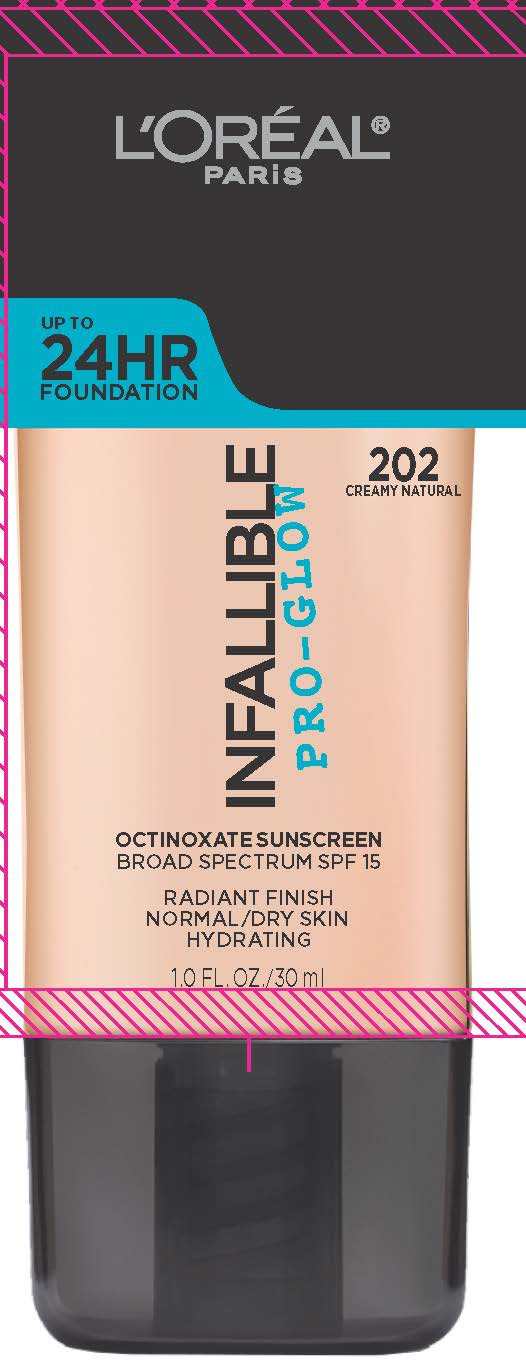 DRUG LABEL: LOreal Paris Infallible ProGlow Broad Spectrum SPF 15 Sunscreen
NDC: 49967-043 | Form: LIQUID
Manufacturer: L'Oreal USA Products Inc
Category: otc | Type: HUMAN OTC DRUG LABEL
Date: 20231229

ACTIVE INGREDIENTS: OCTINOXATE 32 mg/1 mL
INACTIVE INGREDIENTS: WATER; CYCLOMETHICONE 5; ALCOHOL; PHENYL TRIMETHICONE; GLYCERIN; PEG-14 DIMETHICONE; BIS-PEG/PPG-14/14 DIMETHICONE; DIMETHICONE; MAGNESIUM SULFATE, UNSPECIFIED FORM; ETHYLHEXYL HYDROXYSTEARATE; TALC; SILICON DIOXIDE; DISODIUM STEAROYL GLUTAMATE; POLY(METHYL METHACRYLATE; 450000 MW); .ALPHA.-TOCOPHEROL ACETATE; ALUMINUM HYDROXIDE; MAGNESIUM STEARATE; DIPROPYLENE GLYCOL; ALUMINUM OXIDE; BUTYLATED HYDROXYTOLUENE; SODIUM CITRATE; TOCOPHEROL; ISOPROPYL ALCOHOL; TITANIUM DIOXIDE; FERRIC OXIDE RED; BISMUTH OXYCHLORIDE

Drug Facts

Active ingredients

Octinoxate 3.2%

Purpose

Sunscreen

Uses

- helps prevent sunburn

- if used as directed with other sun protection measures (see Directions), decreases the risk of skin cancer and early skin aging caused by the sun

Warnings

For external use only

Flammable until dry.

Do not use near fire, flame or heat.

Do not use

on damaged or broken skin

When using this product

keep out of eyes. Rinse with water to remove.

Stop use and ask a doctor if

rash occurs

Keep out of reach of children.

If swallowed, get medical help or contact a Poison Control Center right away.

Directions

For sunscreen use:

● shake well

● apply liberally 15 minutes before sun exposure

● reapply at least every 2 hours

● use a water resistant sunscreen if swimming or sweating

● Sun Protection Measures. Spending time in the sun increases your risk of skin cancer and early skin aging. To decrease this risk, regularly use a sunscreen with a Broad Spectrum SPF value of 15 or higher and other sun protection measures including:

● limit time in the sun, especially from 10 a.m. – 2 p.m.

● wear long-sleeved shirts, pants, hats, and sunglasses

● children under 6 months of age: Ask a doctor

Other information

protect the product in this container from excessive heat and direct sun

Inactive ingredients

water, cyclopentasiloxane, alcohol denat., phenyl trimethicone, glycerin, PEG-10 dimethicone, bis-PEG/PPG-14/14 dimethicone, dimethicone, magnesium sulfate, ethylhexyl hydroxystearate, talc, silica, PEG/PPG/polybutylene glycol-8/5/3 glycerin, disodium stearoyl glutamate, dimethicone/polyglycerin-3 crosspolymer, polymethyl methacrylate, tocopheryl acetate, aluminum hydroxide, magnesium stearate, silica silylate, dipropylene glycol, alumina, BHT, sodium citrate, tocopherol, isopropyl alcohol; may contain: titanium dioxide, iron oxides, bismuth oxychloride

Questions or comments?

1-800-322-2036

Monday - Friday

(10 a.m. - 5 p.m. EST)